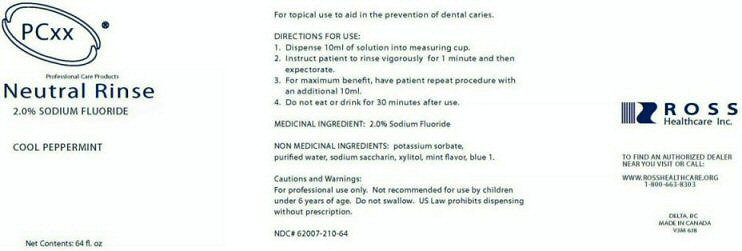 DRUG LABEL: NEUTRAL RINSE
NDC: 62007-210 | Form: LIQUID
Manufacturer: Ross Healthcare, Inc.
Category: prescription | Type: HUMAN PRESCRIPTION DRUG LABEL
Date: 20111018

ACTIVE INGREDIENTS: SODIUM FLUORIDE 2 mL/100 mL
INACTIVE INGREDIENTS: POTASSIUM SORBATE; WATER; SACCHARIN SODIUM DIHYDRATE; XYLITOL

ACTIVE INGREDIENTS SECTION

MEDICINAL INGREDIENT: SODIUM FLUORIDE 2.0%

PURPOSE SECTION

FOR TOPICAL USE TO AID IN THE PREVENTION OF DENTAL CARIES.

CHILDREN SECTION

NOT RECOMMENDED FOR USE BY CHILDREN UNDER 6 YEARS OF AGE.

INDICATIONS AND USE SECTION

AID IN THE PREVENTION OF DENTAL CARIES

WARNINGS SECTION

CAUTIONS AND WARNINGS: FOR PROFESSIONAL USE ONLY. DO NOT SWALLOW. US LAW PROHIBITS DISPENSING WITHOUT PRESCRIPTION.

DOSAGE AND ADMINISTRATION SECTION

DIRECTIONS FOR USE:

1. DISPENSE 10ML OF SOLUTION INTO A MEASURING CUP.

2. INSTRUCT PATIENT TO RINSE VIGOROUSLY FOR I MINUTE AND THEN EXPECTORATE.

3. FOR MAXIMUM BENEFIT, HAVE PATIENT REPEAT PROCEDURE WITH AN ADDITIONAL 10ML.

4. DO NOT EAT OR DRINK FOR 30 MINUTES AFTER USE.

INACTIVE INGREDIENT SECTION

NON MEDICINAL INGREDIENTS: POTASSIUM SORBATE, PURIFIED WATER, SODIUM SACCHARIN, XYLITOL, MINT FLAVOR, BLUE 1.

PACKAGE LABEL

PCxx PROFESSIONAL CARE PRODUCTS NEUTRAL RINSE 2.0% SODIUM FLUORIDE COOL PEPERMINT

NET CONTENTS: 64 FL. OZ

NDC # 62007-210-64

ROSS HEALTHCARE INC. TO FIND AN AUTHORIZED DEALER NEAR YOU VISIT OR CALL WWW.ROSSHEALTHCARE.ORG 1-800-663-8303

DELTA,BC MADE IN CANADA V3M 6J8